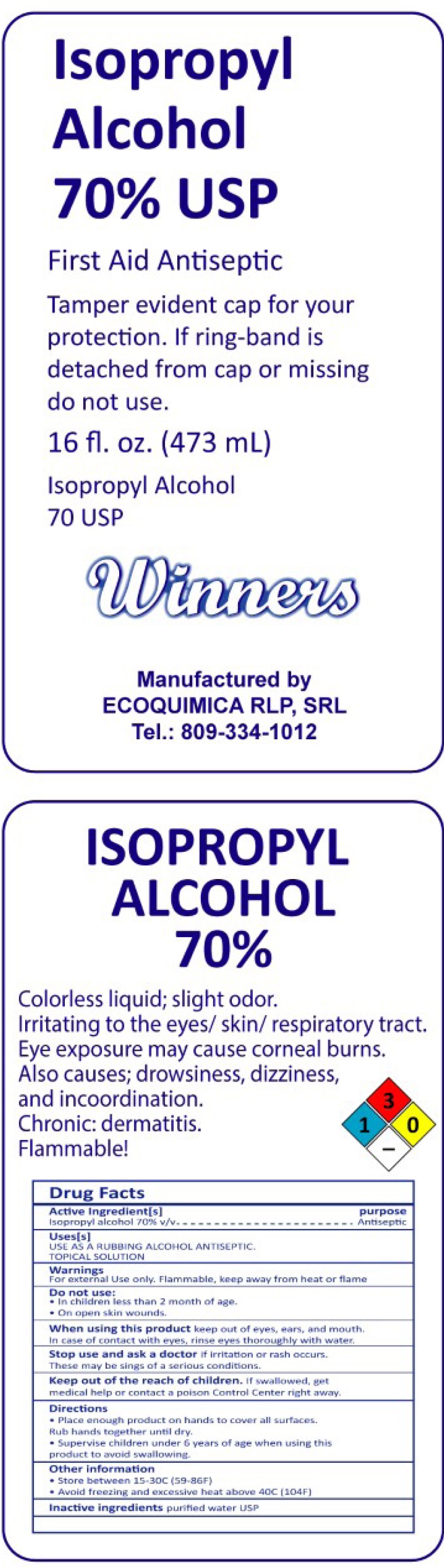 DRUG LABEL: Winner Alcohol
NDC: 79343-000 | Form: LIQUID
Manufacturer: Ecoquimica RLP, S.R.L.
Category: otc | Type: HUMAN OTC DRUG LABEL
Date: 20200812

ACTIVE INGREDIENTS: ISOPROPYL ALCOHOL 0.7 mL/1 mL
INACTIVE INGREDIENTS: WATER

Winner Alcohol

Active Ingredient[s]

Isopropyl alcohol 70% v/v

Purpose

Antiseptic

Uses[s]

USE AS A RUBBING ALCOHOL ANTISEPTIC.

TOPICAL SOLLUTION

Warnings

For external use only. Flammable. Keep away from heat or flame.

Do not use

- in children less than 2 months of age
- on open skin wounds

When using this product

keep out of eyes, ears, and mouth. In case of contact with eyes, rinse eyes thoroughly with water

Stop use and ask a doctor

if irritation or rash occurs. These may be signs of a serious condition.

Keep out of reach of children.

If swallowed, get medical help or contact a Poison Control Center right away

Directions

- Place enough product on hands to cover all surfaces. Rub hands together until dry.
- Supervise children under 6 years of age when using this product to avoid swallowing.

Other information

- Store between 15-30C (59-86F)
- Avoid freezing and excessive heat above 40C (104F)

Inactive ingredients

purified water USP